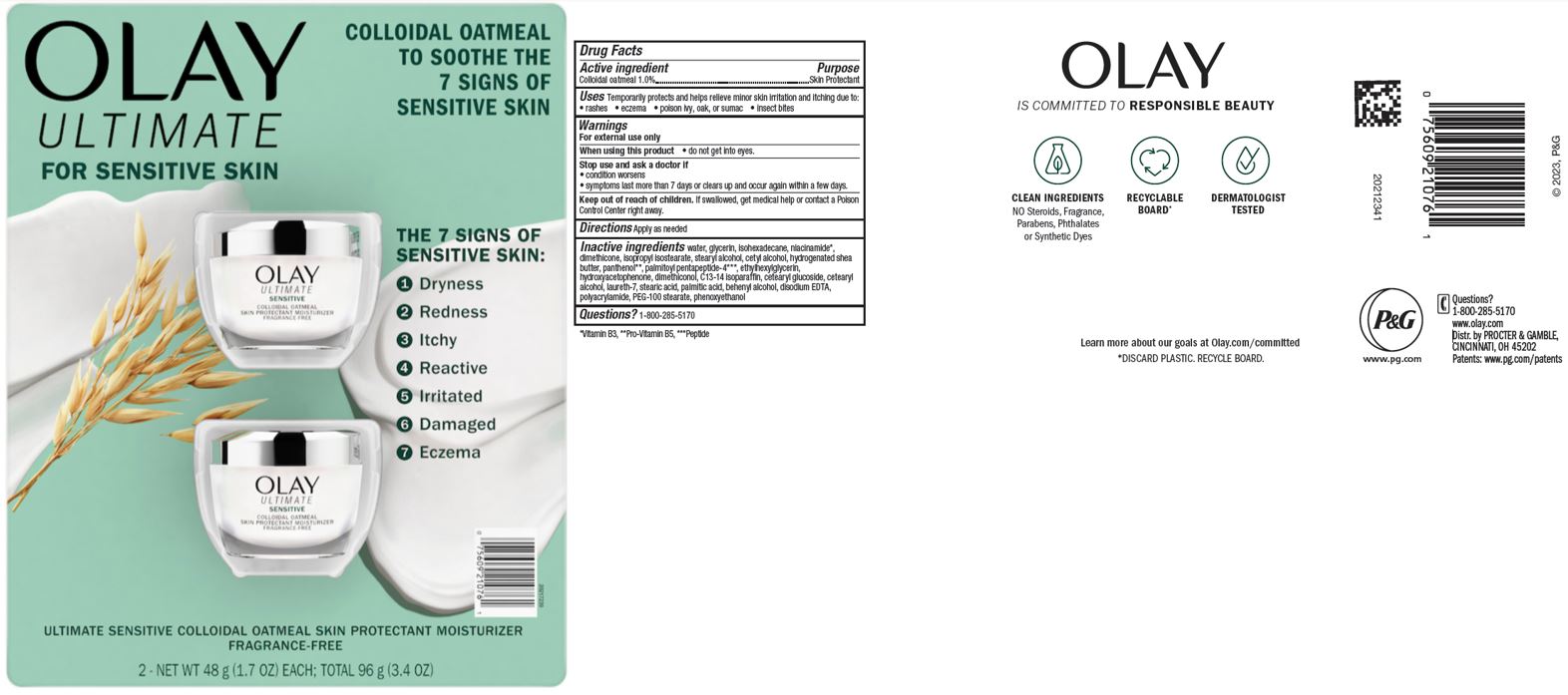 DRUG LABEL: Olay Ultimate Sensitive Colloidal Oatmeal Skin Protectant Moisturizer
NDC: 69423-743 | Form: CREAM
Manufacturer: The Procter & Gamble Manufacturing Company
Category: otc | Type: HUMAN OTC DRUG LABEL
Date: 20251231

ACTIVE INGREDIENTS: OATMEAL 1 g/100 g
INACTIVE INGREDIENTS: PALMITIC ACID; ETHYLHEXYLGLYCERIN; DIMETHICONOL (50000 CST); CETEARYL GLUCOSIDE; ISOHEXADECANE; C13-14 ISOPARAFFIN; SHEA BUTTER; PALMITOYL PENTAPEPTIDE-4; LAURETH-7; NIACINAMIDE; ISOPROPYL ISOSTEARATE; CETYL ALCOHOL; HYDROXYACETOPHENONE; POLYACRYLAMIDE (1300000 MW); DIMETHICONE; EDETATE DISODIUM; PHENOXYETHANOL; WATER; GLYCERIN; STEARIC ACID; PANTHENOL; CETOSTEARYL ALCOHOL; DOCOSANOL; PEG-100 STEARATE; STEARYL ALCOHOL

Olay Ultra Sensitive Colloidal Oatmeal Skin Protectant Moisturizer Fragrance-Free

Drug Facts

Active ingredients

Colloidal Oatmeal 1.0%

Purpose

Skin Protectant

Uses

Temporarily protects and helps relieve minor skin irritation and itching due to:

rashes eczema poison ivy, oak or sumac insect bites

Warnings

For external use only.

Keep out of reach of children. If swallowed, get medical help or contact a Poison Control Center right away.

WHEN USING

Do not get into eyes.

Stop use and ask a doctor if condition worsens, symptoms last more than 7 days or clear up and occur again within a few days

Directions

Apply as needed

INACTIVE INGREDIENT

Water, glycerin, isohexadecane, niacinamide, dimethicone, isopropyl isostearate, stearyl alcohol, cetyl alcohol, hydrogenated shea butter, panthenol, palmitoyl pentapeptide-4, ethylhexylglycerin, hydroxyacetophenone, dimethiconol, C13-14 isoparaffin, cetearyl glucoside, cetearyl alcohol, laureth-7, stearic acid, palmitic acid, behenyl alcohol, disodiumEDTA, polyacrylamide, PEG-100 stearate, phenoxyethanol

Questions:

1-800-285-5170

Manufactured in USA from local and

Imported Ingredients

Distr. by PROCTER & GAMBLE,

CINCINNATI, OH 45202

www.olay.com

PRINCIPAL DISPLAY PANEL - 1.70 oz (48 g)

OLAY ULTIMATE

SENSITIVE

COLLOIDAL OATMEAL

Skin Protectant Moisturizer

FRAGRANCE-FREE

Net Wt. 48 g (1.7 oz)